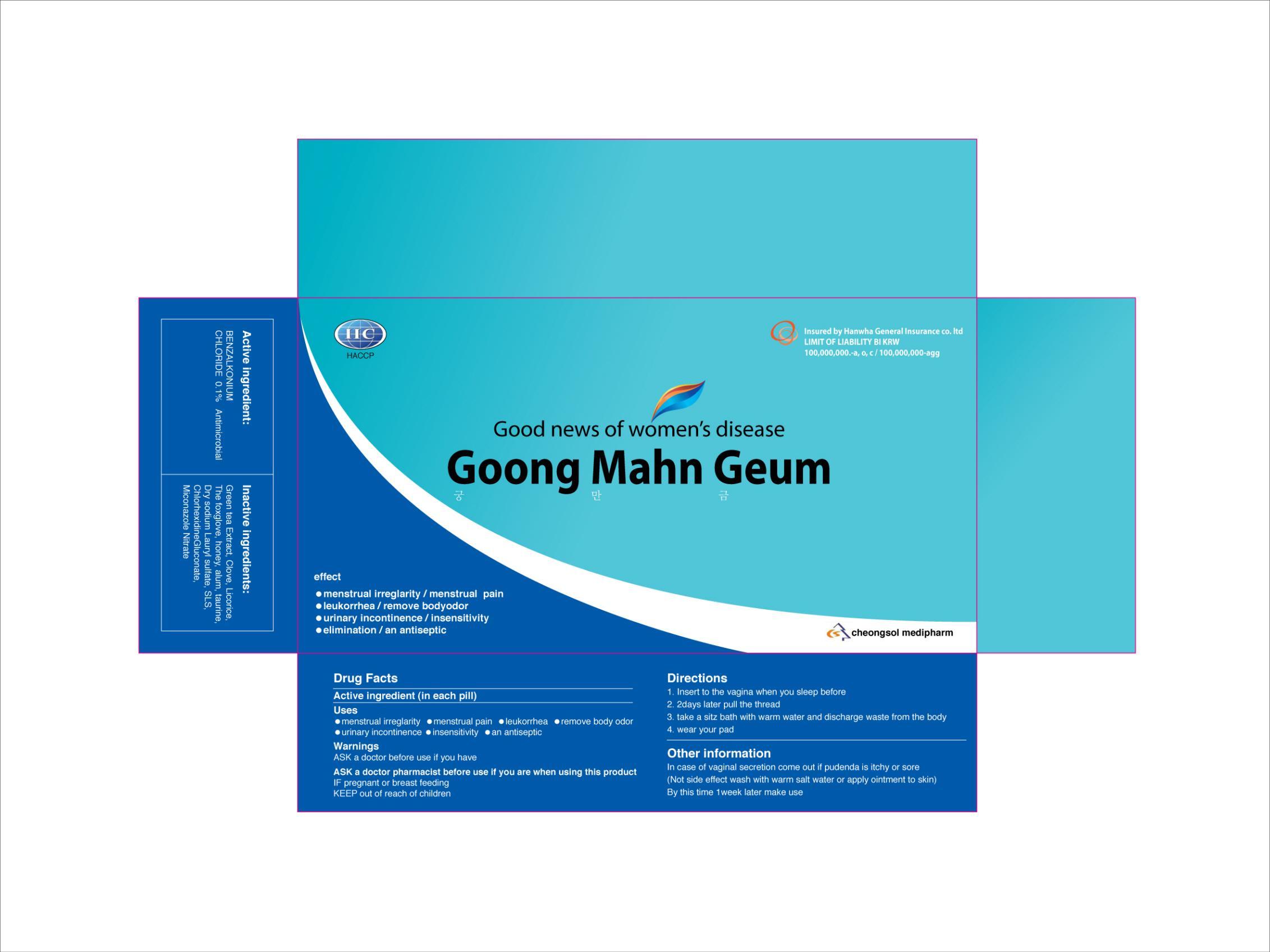 DRUG LABEL: GOONG MAHN GEUM
NDC: 50300-010 | Form: PILL
Manufacturer: CHUNG SOL
Category: otc | Type: HUMAN OTC DRUG LABEL
Date: 20120904

ACTIVE INGREDIENTS: BENZALKONIUM CHLORIDE 0.003 g/1 1
INACTIVE INGREDIENTS: GREEN TEA LEAF; CLOVE; LICORICE; PAULOWNIA TOMENTOSA LEAF; HONEY

ACTIVE INGREDIENT

Active ingredient: BENZALKONIUM CHLORIDE 0.1%

INACTIVE INGREDIENT

Inactive ingredients:
Green tea Extract, Clove, Licorice, The foxglove, honey, alum, taurine, Dry sodium Lauryl sulfate,SLS, Chlorhexidine Gluconate

PURPOSE

Uses:
menstrual irreglarity, menstrual pain, leukorrhea, remove body odor, urinary incontinence, insensitivity, an antiseptic

WARNINGS

ASK a doctor before use if you have
ASK a doctor pharmacist before use if you are when using this product
IF pregnant or breast feeding
KEEP out of reach of children

Other information
In case of vaginal secretion come out if pudenda is itchy or sore
- Not side effect wash with warm salt water or apply ointment to skin
By thistime 1week later make use

KEEP OUT OF REACH OF CHILDREN

INDICATIONS AND USAGE

Indication and usage:
1. Insert to the vagina when you sleep before
2. 2days later pull the thread
3. take a sitz bath with warm water and discharge waste from the body
4. wear your pad

DOSAGE AND ADMINISTRATION

Directions:
1. Insert to the vagina when you sleep before
2. 2days later pull the thread
3. take a sitz bath with warm water and discharge waste from the body
4. wear your pad